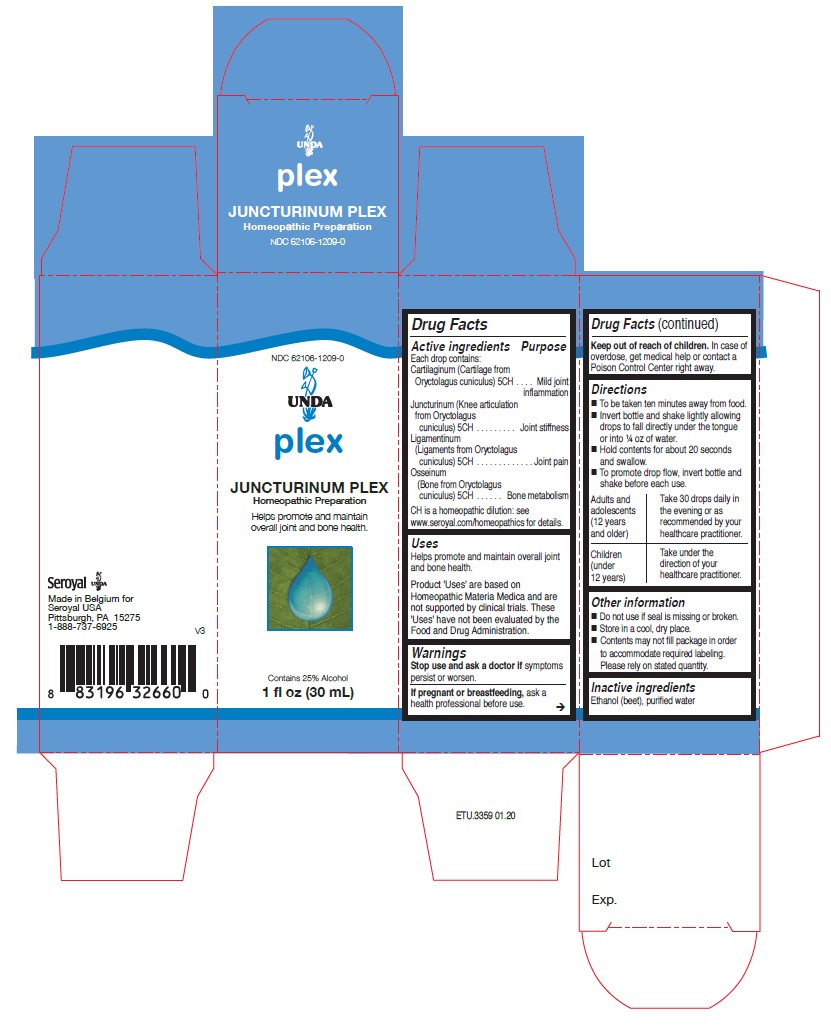 DRUG LABEL: JUNCTURINUM PLEX
NDC: 62106-1209 | Form: LIQUID
Manufacturer: Seroyal USA
Category: homeopathic | Type: HUMAN OTC DRUG LABEL
Date: 20210715

ACTIVE INGREDIENTS: ORYCTOLAGUS CUNICULUS KNEE JOINT 5 [hp_C]/30 mL; ORYCTOLAGUS CUNICULUS LIGAMENT 5 [hp_C]/30 mL; ORYCTOLAGUS CUNICULUS BONE 5 [hp_C]/30 mL; ORYCTOLAGUS CUNICULUS CARTILAGE 5 [hp_C]/30 mL
INACTIVE INGREDIENTS: WATER; ALCOHOL

JUNCTURINUM PLEX

Active ingredients

Each drop contains equal parts of:
Cartilaginum (Cartilage from Oryctolagus cuniculus) 5CH
Juncturinum (Knee articulation from Oryctolagus cuniculus) 5CH
Ligamentinum (Ligaments from Oryctolagus cuniculus) 5CH
Osseinum (Bone from Oryctolagus cuniculus) 5CH

Uses
Helps promote and maintain overall joint and bone health.

Warnings
Stop use and ask a doctor if symptoms persist or worsen.

If pregnant or breastfeeding, ask a health professional before use.

Keep out of reach of children.

In case of overdose, get medical help or contact a Poison Control Center right away.

Stop use and ask a doctor if symptoms persist or worsen.

PREGNANCY OR BREAST FEEDING

If pregnant or breastfeeding, ask a health professional before use.

Keep out of reach of children.

OVERDOSAGE

In case of overdose, get medical help or contact a Poison Control Center right away.

Other information
Do not use if seal is missing or broken.
Store in a cool, dry place.

Contents may not fill package in order to accommodate required labeling. Please rely on stated quantity.

Inactive ingredients
Ethanol (beet), purified water

Directions

To be taken ten minutes away from food.
Invert bottle and shake lightly allowing drops to fall directly under the tongue or into ¼ oz of water.
Hold contents for about 20 seconds and swallow.
To promote drop flow, invert bottle and shake before each use.

Adults and adolescents (12 years and older)

Take 30 drops daily in the evening or as recommended by your healthcare practitioner.

Children (under 12 years)

Take under the direction of your healthcare practitioner.

Uses
Helps promote and maintain overall joint and bone health.

Directions

To be taken ten minutes away from food.
Invert bottle and shake lightly allowing drops to fall directly under the tongue or into ¼ oz of water.
Hold contents for about 20 seconds and swallow.
To promote drop flow, invert bottle and shake before each use.

Adults and adolescents (12 years and older)

Take 30 drops daily in the evening or as recommended by your healthcare practitioner.

Children (under 12 years)

Take under the direction of your healthcare practitioner.

PACKAGE LABEL

NDC 62106-1209-0

UNDA

Plex

JUNCTURINUM PLEX

Homeopathic Preparation

To promote and maintain overall joint and bone health.

Contains 25% Alcohol
1 fl oz (30 mL)